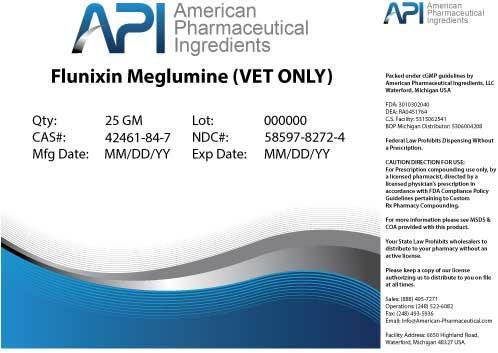 DRUG LABEL: Flunixin Meglumine
NDC: 58597-8272 | Form: POWDER
Manufacturer: AMERICAN PHARMACEUTICAL INGREDIENTS LLC
Category: other | Type: BULK INGREDIENT
Date: 20140425

ACTIVE INGREDIENTS: Flunixin Meglumine 1 g/1 g

Flunixin Meglumine